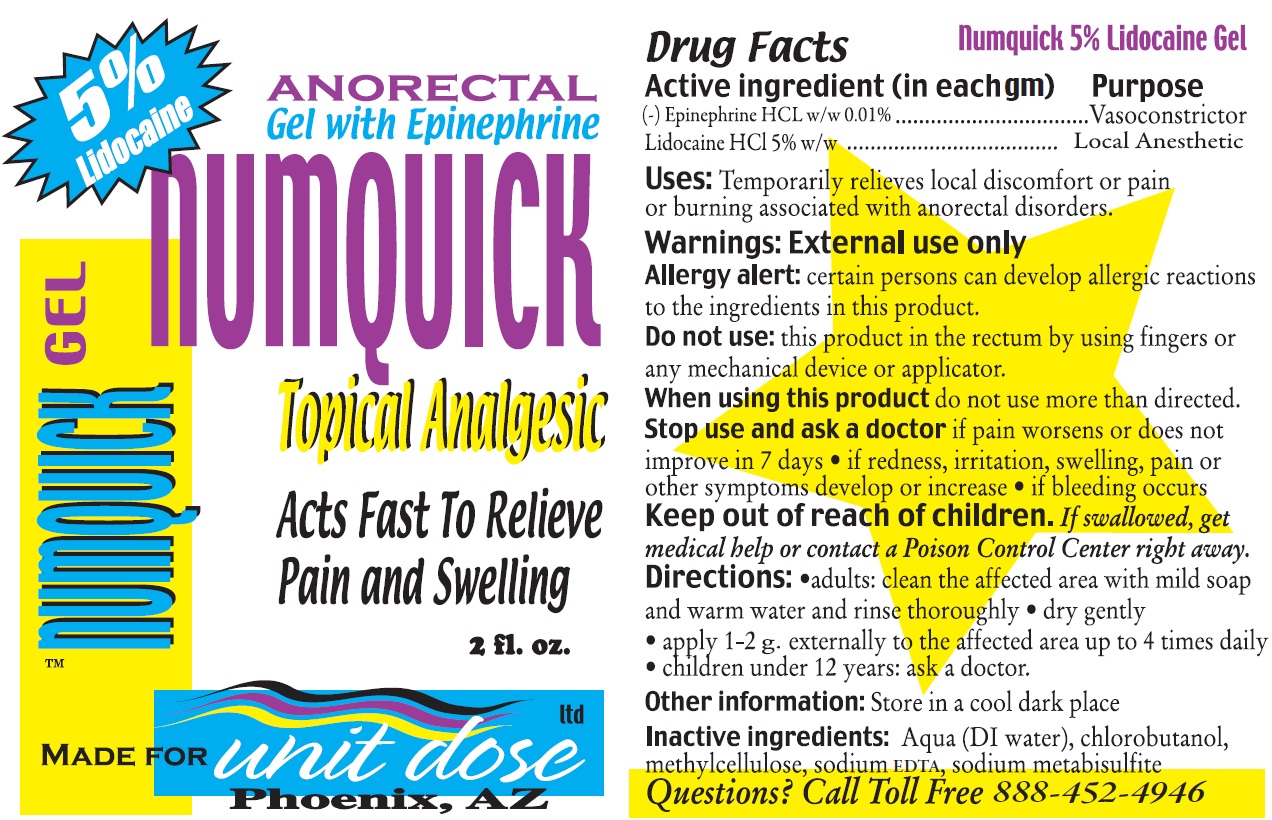 DRUG LABEL: Numquick Topical Analgesic
NDC: 67194-005 | Form: GEL
Manufacturer: Unit Dose, Ltd.
Category: otc | Type: HUMAN OTC DRUG LABEL
Date: 20231019

ACTIVE INGREDIENTS: EPINEPHRINE HYDROCHLORIDE 0.1 mg/1 mL; LIDOCAINE HYDROCHLORIDE 50 mg/1 mL
INACTIVE INGREDIENTS: WATER; CHLOROBUTANOL; EDETATE SODIUM; SODIUM METABISULFITE

Numquick Topical Analgesic

Active ingredient

(-) Epinephrine HCL w/w 0.01%

Lidocaine HCl 5% w/w

Purpose

Vasoconstrictor

Local Anesthetic

Uses:

Temporarily relieves local discomfort or pain or burning associated with anorectal disorders.

Warnings:

External use only

certain persons can develop allergic reactions to the ingredients in this product. Allergy alert:

Do not use:

this product in the rectum by using fingers or any mechnical device or applicator.

When using this product

do not use more than directed.

Stop use and ask a doctor

if pain worsens or does notimprove in 7 days

- if redness, irritation, swelling, pain or other symptoms develop or increase
- if bleeding occurs

Keep out of reach of children.

If swallowed, get medical help or contact a Poison Control Center right away.

Directions:

- adults: clean the affected area with mild soap and warm water and rinse thoroughly
- dry gently
- apply 1-2 g. externally to the affected area up to 4 times daily
- children under 12 years: ask a doctor.

Other information:

Store in a cool dark place

Inactive ingredients:

Aqua (DI water), chlorobutanol, methylcellulose, sodium EDTA, sodium metabisulfite

Questions?

Call Toll Free 888-452-4946